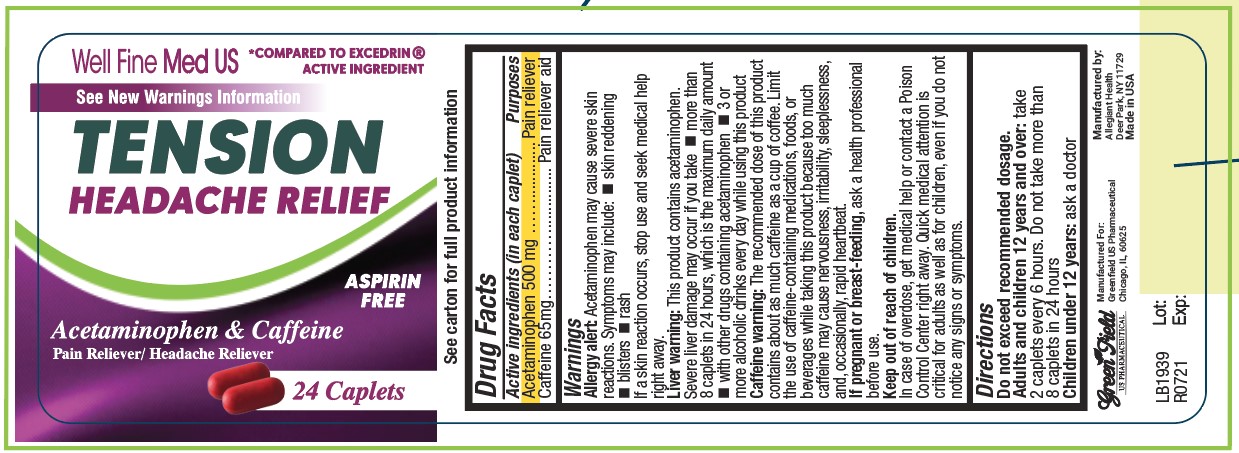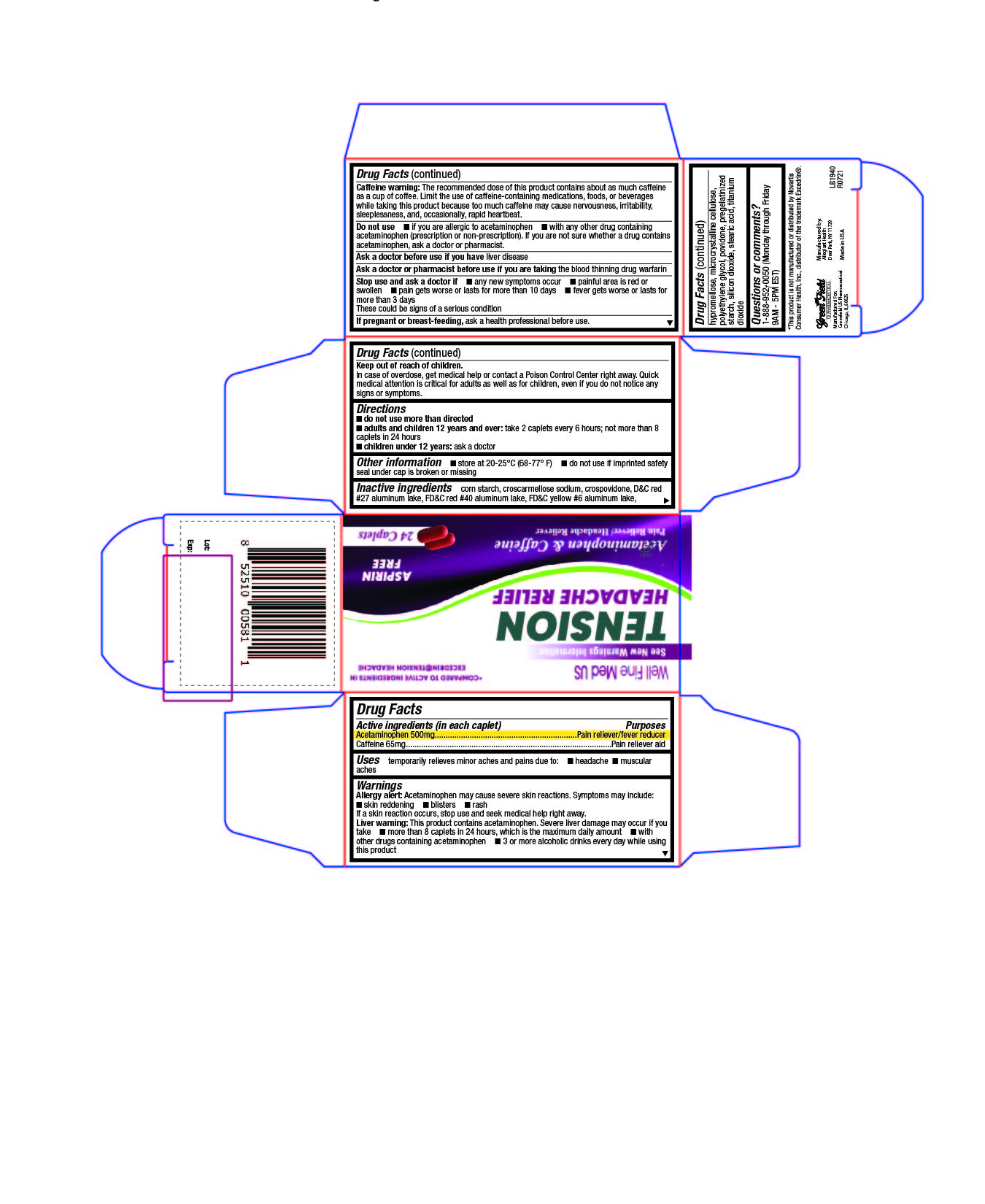 DRUG LABEL: Tension Headache Relief
NDC: 69168-001 | Form: CAPSULE, COATED
Manufacturer: Allegiant Health
Category: otc | Type: HUMAN OTC DRUG LABEL
Date: 20211122

ACTIVE INGREDIENTS: ACETAMINOPHEN 500 mg/1 1; CAFFEINE 65 mg/1 1
INACTIVE INGREDIENTS: STARCH, CORN; CROSCARMELLOSE SODIUM; CROSPOVIDONE; D&C RED NO. 27 ALUMINUM LAKE; FD&C RED NO. 40; FD&C YELLOW NO. 6; HYPROMELLOSE, UNSPECIFIED; MICROCRYSTALLINE CELLULOSE; POLYETHYLENE GLYCOL, UNSPECIFIED; POVIDONE; SILICON DIOXIDE; STEARIC ACID; TITANIUM DIOXIDE

GreenField - Tension Headache

Active ingredient(s)

Acetaminophen 500 mg
Caffeine 65mg

Purpose

Pain reliever
Pain reliever aid

Use(s)

temporarily relieves minor aches and pains due to:

- headache

- muscular aches

Warnings

Liver warning: This product contains acetaminophen. Severe liver damage may occur if you ■ take more than 8 tablets in 24 hours, which is the maximum daily amount ■ take with other drugs containing acetaminophen ■ have 3 or more alcoholic drinks every day while using this product

Allergy alert: Aspirin may cause a severe allergic reaction which may include: ■ hives ■ facial swelling ■ asthma (wheezing) ■ shock
Acetaminophen may cause severe skin reactions. Symptoms may include: ■ skin reddening ■ blisters ■ rash
If a skin reaction occurs, stop use and seek medical help right away.

Caffeine warning: The recommended dose of this product contains about as much caffeine as a cup of coffee. Limit the use of caffeine-containing medications, foods, or beverages while taking this product because too much caffeine may cause nervousness, irritability, sleeplessness, and occasionally rapid heartbeat.

Do not use

- if you are allergic to acetaminophen
- with any other drug containing acetaminophen (prescription or non-prescription). If you are not sure whether a drug contains
  acetaminophen, ask a doctor or pharmacist.

Ask a doctor before use if

you have liver disease

Ask a doctor or pharmacist before use if

you are taking the blood thinning drug warfarin

Stop use and ask a doctor if

- any new symptoms occur
- painful area is red or swollen
- pain gets worse or lasts for more than 10 days
- fever gets worse or lasts for more than 3 days

These could be signs of a serious condition.

Pregnancy/Breastfeeding

If pregnant or breast-feeding, ask a health professional before use.

Keep out of reach of children

In case of overdose, get medical help or contact a Poison Control Center right away. Quick
medical attention is critical for adults as well as for children, even if you do not notice any
signs or symptoms.

Directions

Do not use more than directed

Adults and children 12 years and over: take 2 caplets every 6 hours; not more than 8 caplets in 24 hours

Children under 12 years: ask a doctor

Other information

- Store at 20-25°C (68-77° F)

- Do not use if imprinted safety seal under cap is broken or missing

Inactive ingredients

corn starch, croscarmellose sodium, crospovidone, D&C red #27 aluminum lake, FD&C red #40
aluminum lake, FD&C yellow #6 aluminum lake, hypromellose, microcrystalline cellulose, polyethylene glycol, povidone,
pregelatinized starch, silicon dioxide, stearic acid, titanium dioxide

Questions

1-888-952-0050 (Monday through Friday 9AM - 5PM EST

Principal Display Panel

Tension Headache
Tension Headache